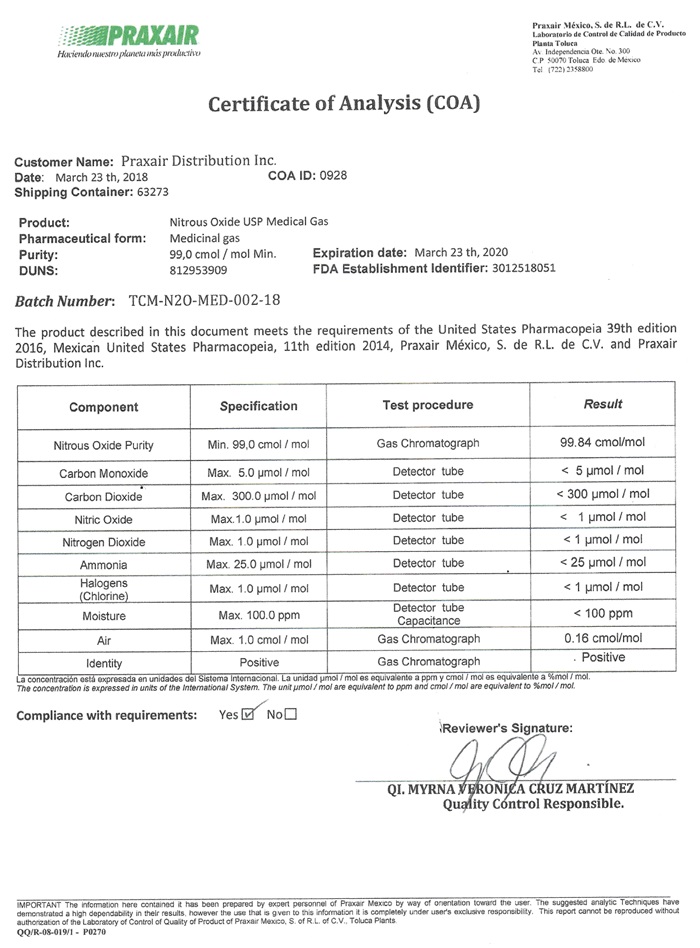 DRUG LABEL: NITROUS OXIDE
NDC: 72223-001 | Form: GAS
Manufacturer: Praxair Mexico, S. de R.L. de C.V
Category: prescription | Type: HUMAN PRESCRIPTION DRUG LABEL
Date: 20211109

ACTIVE INGREDIENTS: NITROUS OXIDE 990 mL/1 L

Nitrous Oxide

NITROUS OXIDE USP LABEL

PRAXAIR Praxair Mexico S. de, R.L. de C.V.

Laboraicarlo de Costrel de Calidad de Producto

Plasia Toluca

Av Independence Ote No 300

CP 50070 Toluca Ede de Mexico

Tel (722)2358800

Certificate of Analysis (COA)

Customer Name: Praxair Distribution Inc.

Date: March 23 th, 2018 COA US 0928

Shipping Container: 63273

Product: Nitrous Oxide USP Medical Gas

Pharmaceutical form: Medicinal gas

Purity: 99.0 cmol/ mol Min. Expiration Date: March 23 th, 2020

DUNS: 8129539029 FDA Establishment Identifier: 3012518051

Batch Number: TCM-N20-MED-002-18

This product described in this document meets the requirements of the United States Pharmacopeia 39th edition 2016, Mexican United States Pharmacopeia, 11th edition 2014, Praxair Mexico, S. de R.L. de C.V. and Praxair Distribution, Inc.

Component Specification Test Procedure Results

Nitrous Oxide Purity Min. 99.0 cmol/moi Gas Chromatograph 99.84 cmol/mol

Carbon Monoxide Max. 5.0 µmol/mol Detector tube < 5 µmol/mol

Carbon Dioxide Max. 300.0 µmol/mol Detector tube < 300 µmol/mol

Nitric Oxide Max. 1.0 µmol/mol Detector tube < 1 µmol/mol

Nitrogen Dioxide Max. 1.0 µmol/mol Detector tube < 1 µmol/mol

Ammonia Max. 25.0 µmol/mol Detector tube < 25 µmol/mol

Halogens

(Chlorine) Max. 1.0 µmol/mol Detector tube < 1 µmol/mol

Moisture Max. 100.0 ppm Detector tube < 100 ppm

Capacitance

Air Max 1.0 cmol/mol Gas Chromatograph 0.16 cmol/mol

Identity Positive Gas Chromatograph Positive

La concentracion esto expresada en unidades del Sistoma Internaciona La unidad µmol/mol

Es equivalente a porm y cmol/ mol es equivalente a %mol/mol.

The concentration is expressed in units of the International System. The unit µmol/mol are equivalent to ppm and cmol/mol are equivalent to % mol/mol.

Compliance with requirements: Yes _X_ No ___

Reviewer’s Signature:

____________________________________________

QI. MYRNA VEONICA CRUZ MARTINEZ

Quality Control Responsible.

IMPORTANT The information here contained it has been prepared by expert personnel of Praxair Mexico by way of orientation toward the user. The suggested analytic Techniques have demonstrated a high dependability I their results, however, the use that is given to the information it is completely user user’s exclusive responsibility. This report cannot be reportability. This report cannot be reproduced without authorization of the Laboratory of Coontrol of Quality of Product of Praxair Mexidom, S. de, R.L. de C.V., Toluca Plants.

QQ/r-08-019/1 – P0270